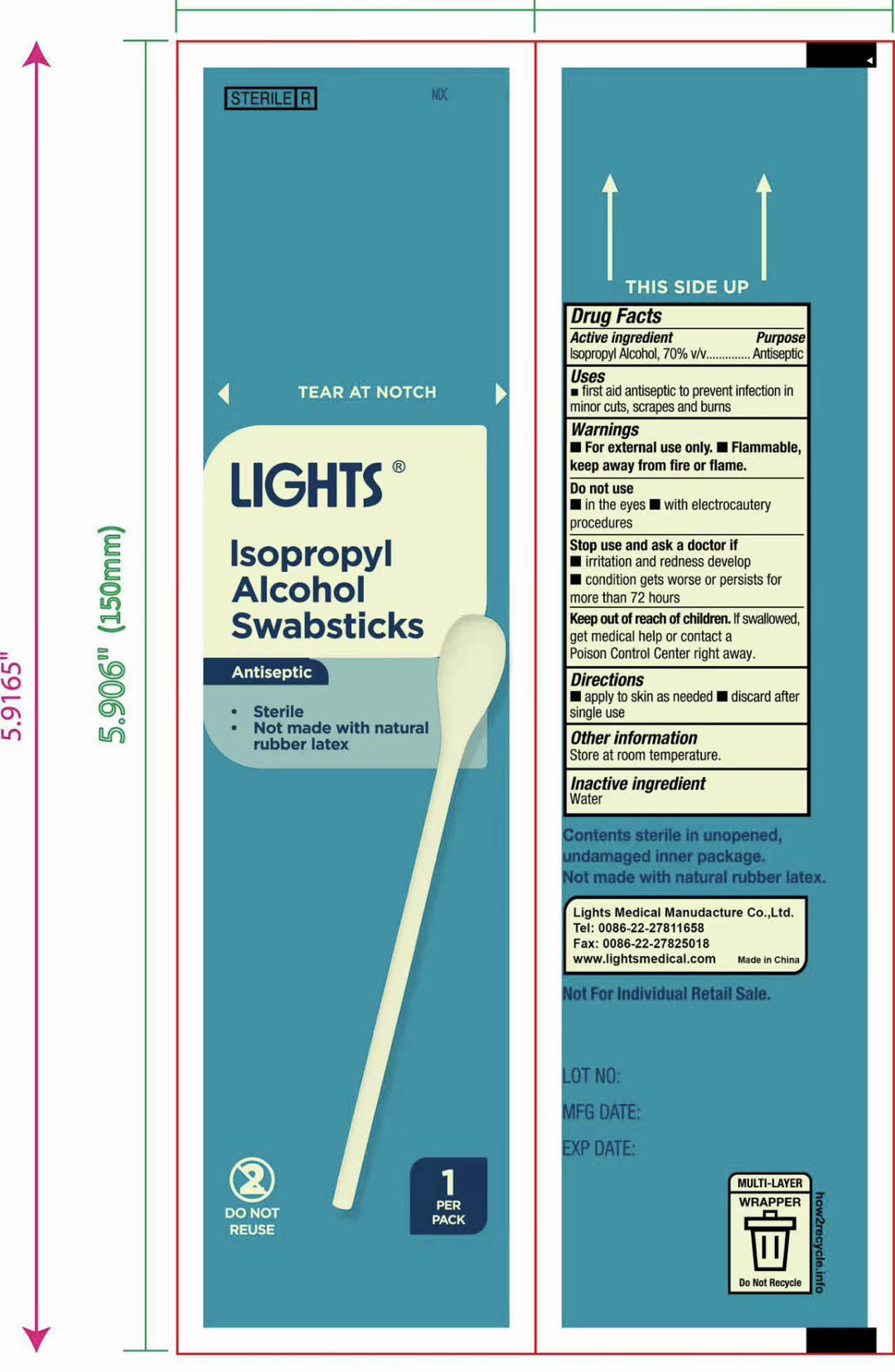 DRUG LABEL: Lights Swabsticks
NDC: 61333-217 | Form: SOLUTION
Manufacturer: Lights Medical Manufacture Co., Ltd.
Category: otc | Type: HUMAN OTC DRUG LABEL
Date: 20251122

ACTIVE INGREDIENTS: ISOPROPYL ALCOHOL 70 mL/100 mL
INACTIVE INGREDIENTS: WATER

Lights 61333-217 IPA swabstick

Active Ingredient:

Isopropyl Acohol 70% v/v

Purpose:

Antiseptic

Use:

First aid antiseptic to help prevent infection in minor cuts, scrapes and burns.

Warnings:

- For external use only
- Flammable, keep away from fire or flame

Do not use

- in the eyes
- with electrocautery procedures

Stop use and ask a doctor if

- irritation and redness develop
- condition gets worse or persist for more than 72 hours

Keep out of reach of children. If swallowed, get medical help or contact a Poison Control Center right away

Directions

- apply to skin as needed
- discard after single use

Other information

- Store at room temperature

Inactive Ingredient

Water